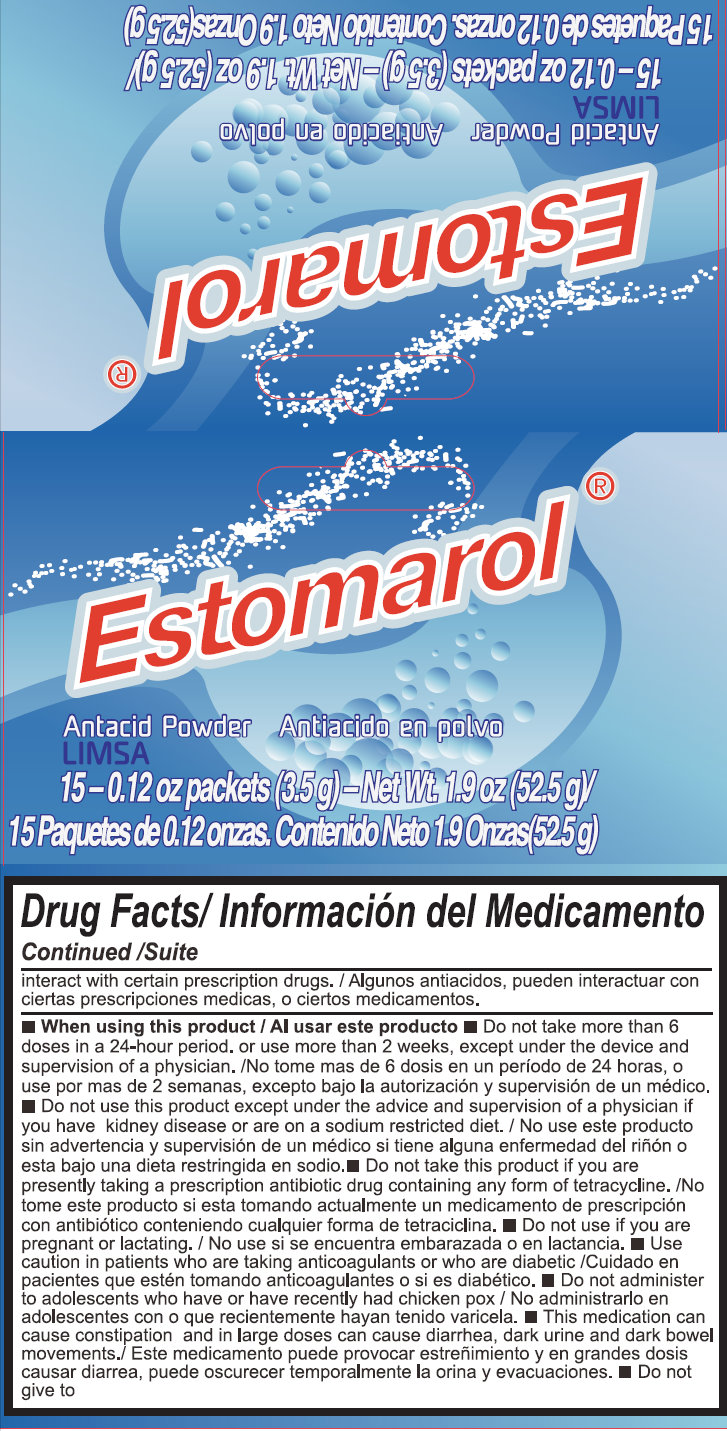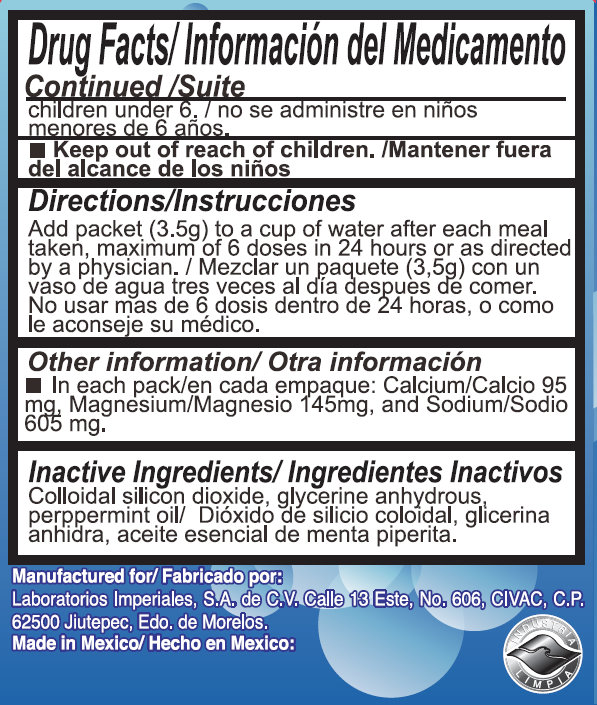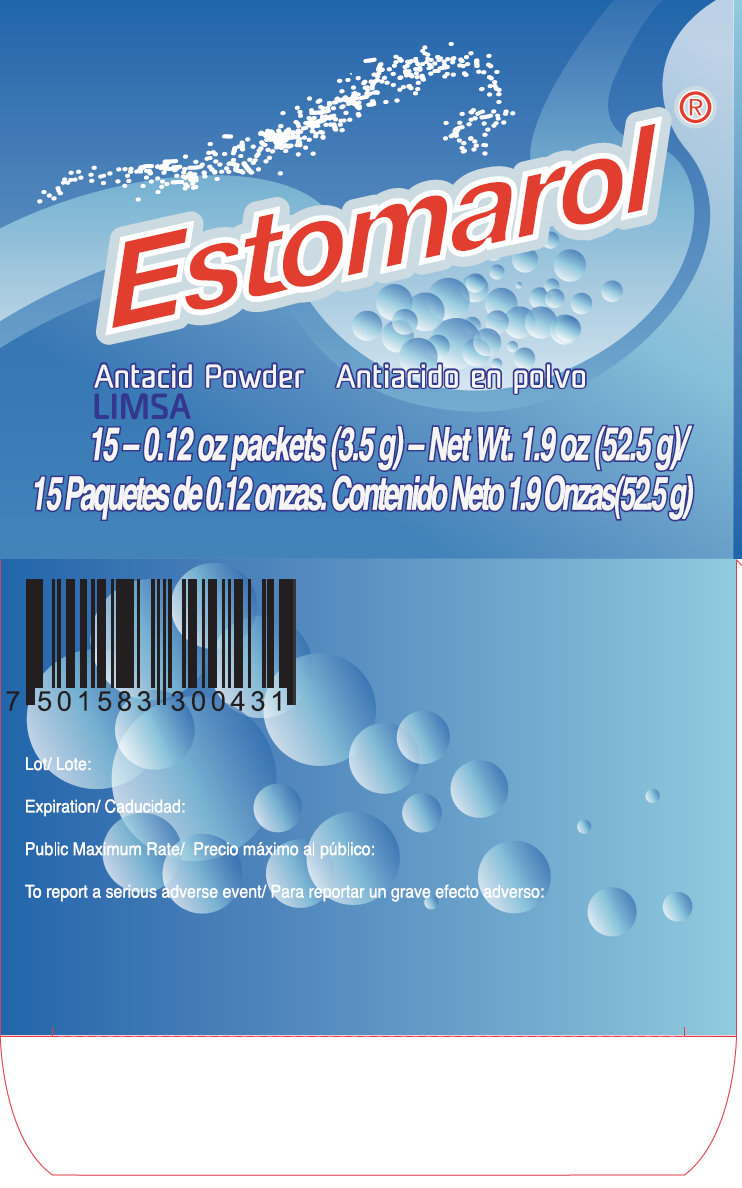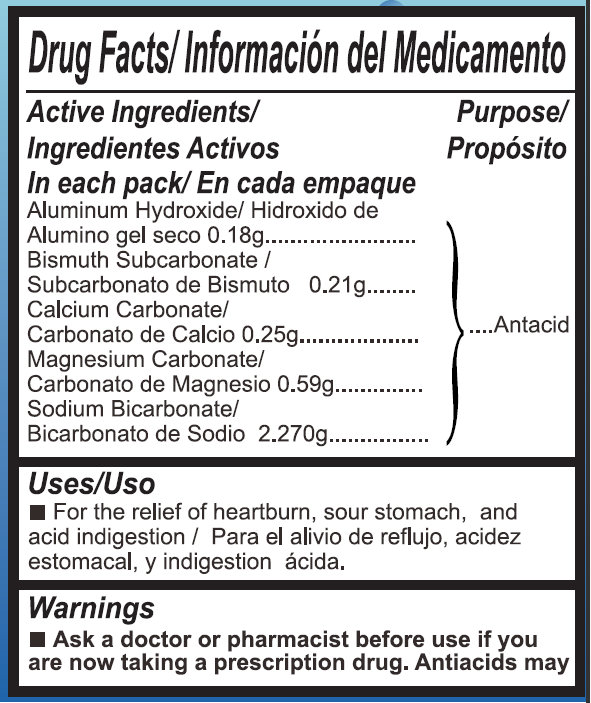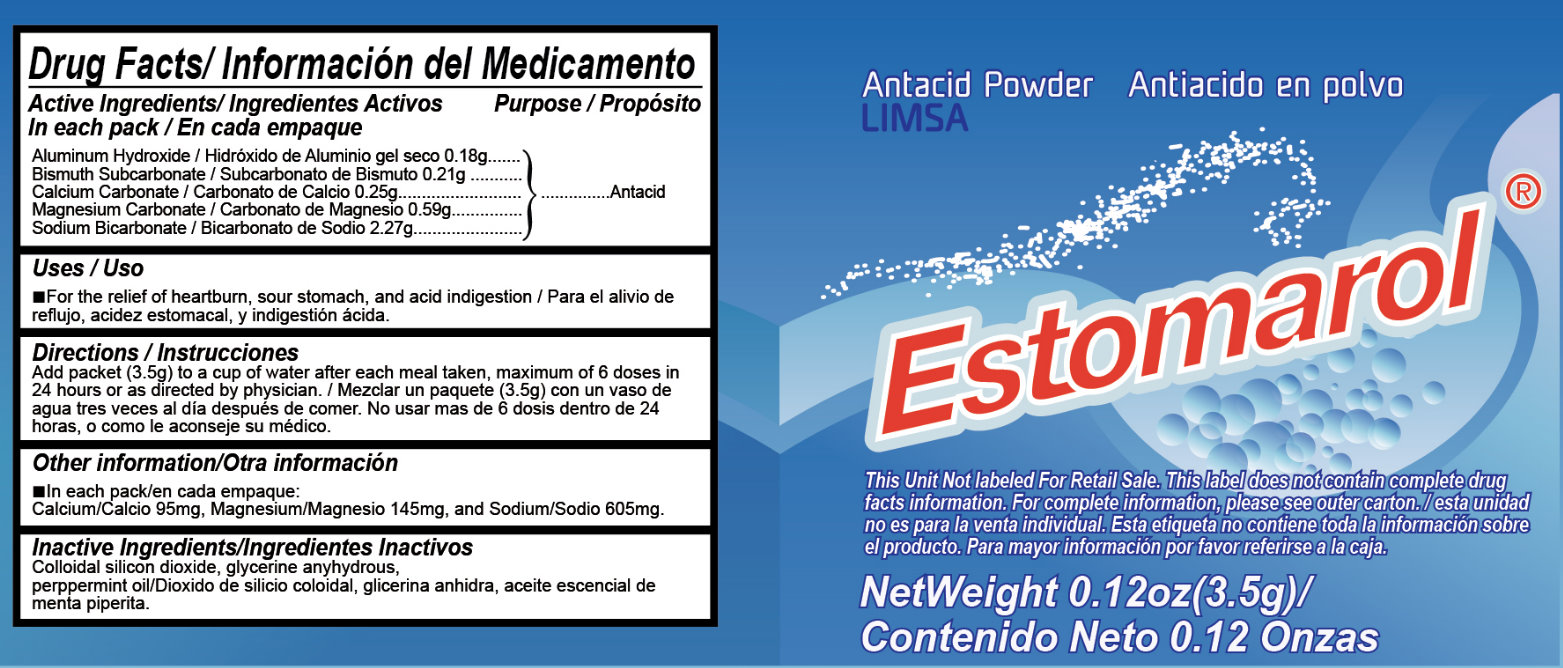 DRUG LABEL: Estomarol
NDC: 57465-100 | Form: POWDER
Manufacturer: Laboratorios Imperiales, S.A. de C.V.
Category: otc | Type: HUMAN OTC DRUG LABEL
Date: 20191224

ACTIVE INGREDIENTS: ALUMINUM HYDROXIDE 0.18 g/3.5 g; BISMUTH SUBCARBONATE 0.21 g/3.5 g; CALCIUM CARBONATE 0.25 g/3.5 g; MAGNESIUM CARBONATE 0.59 g/3.5 g; SODIUM BICARBONATE 2.27 g/3.5 g
INACTIVE INGREDIENTS: SILICON DIOXIDE; GLYCERIN

Estomarol Antacid Powder

Drug Facts

Active Ingredients

In each pack

Aluminum Hydroxide 0.18g

Bismuth Subcarbonate 0.21g

Calcium Carbonate 0.25g

Magnesium Carbonate 0.59g

Sodium Bicarbonate 2.27g

Purpose

Antacid

Uses

- For the relief of heartburn, sour stomach, and acid indigestion

Directions

Add packet (3.5g) to a cup of water after each meal taken, maximum of 6 doses in 24 hours or as directed by a physician.

Other information

In each pack:

Calcium 95mg, Magnesium 145mg, and Sodium 605mg.

Inactive Ingredients

Colloidal silicon dioxide, glycerine anyhydrous, peppermint oil

Warnings

- Ask a doctor or pharmacist before use if you are now taking a prescription drug. Antacids may interact with certain prescription drugs.

When using this product

- Do not take more than 6 doses in 24-hour period, or use more than 2 weeks, except under the advice and supervision of a physician.
- Do not use this product except under the advice and supervision of a physician if you have kidney disease or are on a sodium restricted diet.
- Do not take this product if you are presently taking a prescription antibiotic drug containing any form of tetracycline.
- Do not use if you are pregnant or lactating.
- Use caution in patients who are taking anticoagulants or who are diabetic.
- Do not administer to adolescents who have or have recently had chicken pox
- This medication can cause constipation and in large doses can cause diarrhea, dark urine and dark bowel movements.
- Do not give to children under 6

Keep out of reach of children.

PACKAGE LABEL

Estomarol

Antacid Powder

LIMSA

15-0.12 oz packets (3.5g) - Net Wt. 1.9 oz (52.5 g)